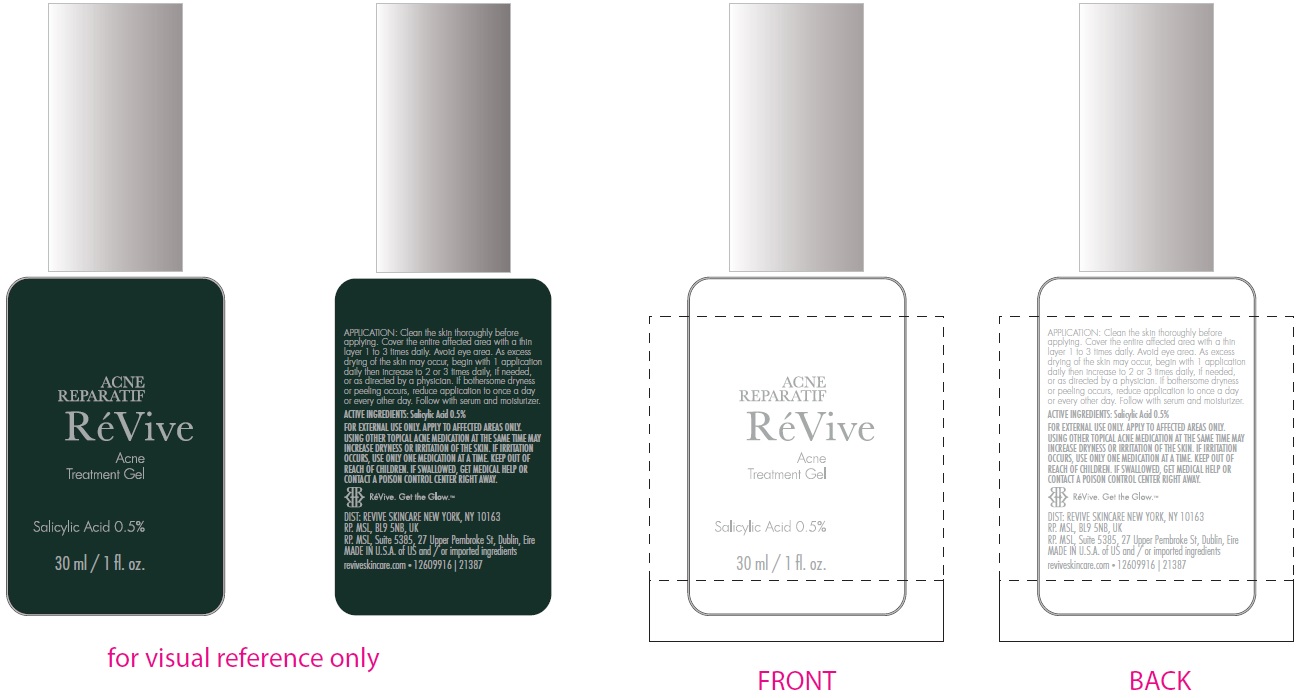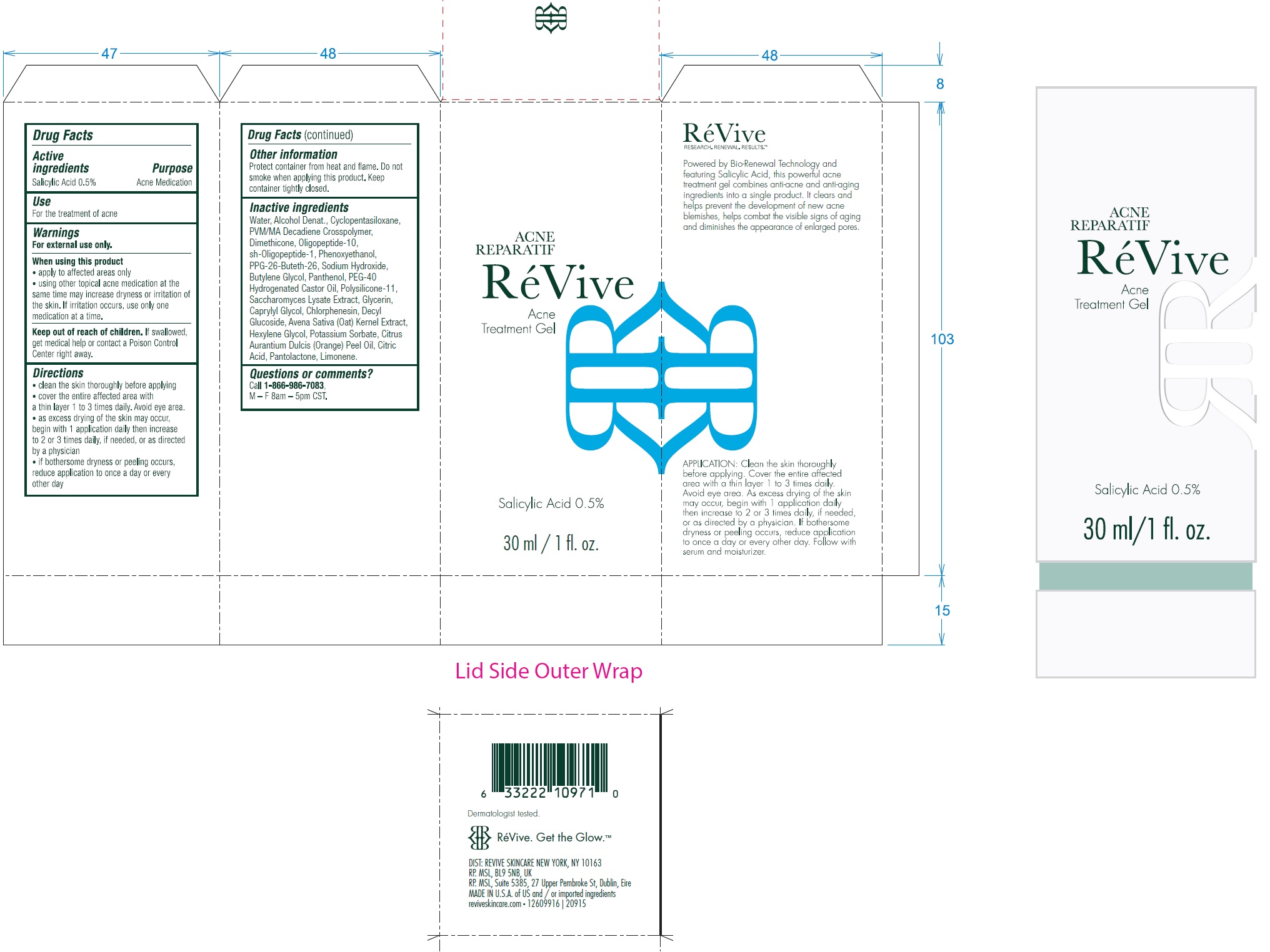 DRUG LABEL: Acne Reparatif
NDC: 82691-140 | Form: GEL
Manufacturer: RV Skincare LLC
Category: otc | Type: HUMAN OTC DRUG LABEL
Date: 20231106

ACTIVE INGREDIENTS: SALICYLIC ACID 5 mg/1 mL
INACTIVE INGREDIENTS: WATER; ALCOHOL; CYCLOMETHICONE 5; DIMETHICONE; OLIGOPEPTIDE-10; NEPIDERMIN; PHENOXYETHANOL; PPG-26-BUTETH-26; SODIUM HYDROXIDE; BUTYLENE GLYCOL; PANTHENOL; POLYOXYL 40 HYDROGENATED CASTOR OIL; DIMETHICONE/VINYL DIMETHICONE CROSSPOLYMER (SOFT PARTICLE); SACCHAROMYCES LYSATE; GLYCERIN; CAPRYLYL GLYCOL; CHLORPHENESIN; DECYL GLUCOSIDE; OAT; HEXYLENE GLYCOL; POTASSIUM SORBATE; ORANGE OIL, COLD PRESSED; CITRIC ACID MONOHYDRATE; PANTOLACTONE, (R)-; LIMONENE, (+)-

Acne Reparatif

Active ingredients

Salicylic Acid 0.5%

Purpose

Acne Medication

Use

For the treatment of acne

Warnings

For external use only.

When using this product

- apply to affected areas only
- using other topical acne medication at the same time may increase dryness or irritation of the skin. If irritation occurs, use only one medication at a time.

Keep out of reach of children.

If swallowed, get medical help or contact a Poison Control Center right away.

Directions

- clean the skin thoroughly before applying
- cover the entire affected area with a thin layer 1 to 3 times daily. Avoid eye area.
- as excess drying of the skin may occur, begin with 1 application daily then increase to 2 or 3 times daily, if needed, or as directed by a physician
- if bothersome dryness or peeling occurs, reduce application to once a day or every other day

Other information

Protect container from heat and flame. Do not smoke when applying this product. Keep container tightly closed.

Inactive ingredients

Water, Alcohol Denat., Cyclopentasiloxane, PVM/MA Decadiene Crosspolymer, Dimethicone, Oligopeptide-10, sh-Oligopeptide-1, Phenoxyethanol, PPG-26-Buteth-26, Sodium Hydroxide, Butylene Glycol, Panthenol, PEG-40 Hydrogenated Castor Oil, Polysilicone-11, Saccharomyces Lysate Extract, Glycerin, Caprylyl Glycol, Chlorphenesin, Decyl Glucoside, Avena Sativa (Oat) Kernel Extract, Hexylene Glycol, Potassium Sorbate, Citrus Aurantium Dulcis (Orange) Peel Oil, Citric Acid, Pantolactone, Limonene.

Questions or comments?

Call , M - F 8am - 5 pm CST. 1-866-986-7083